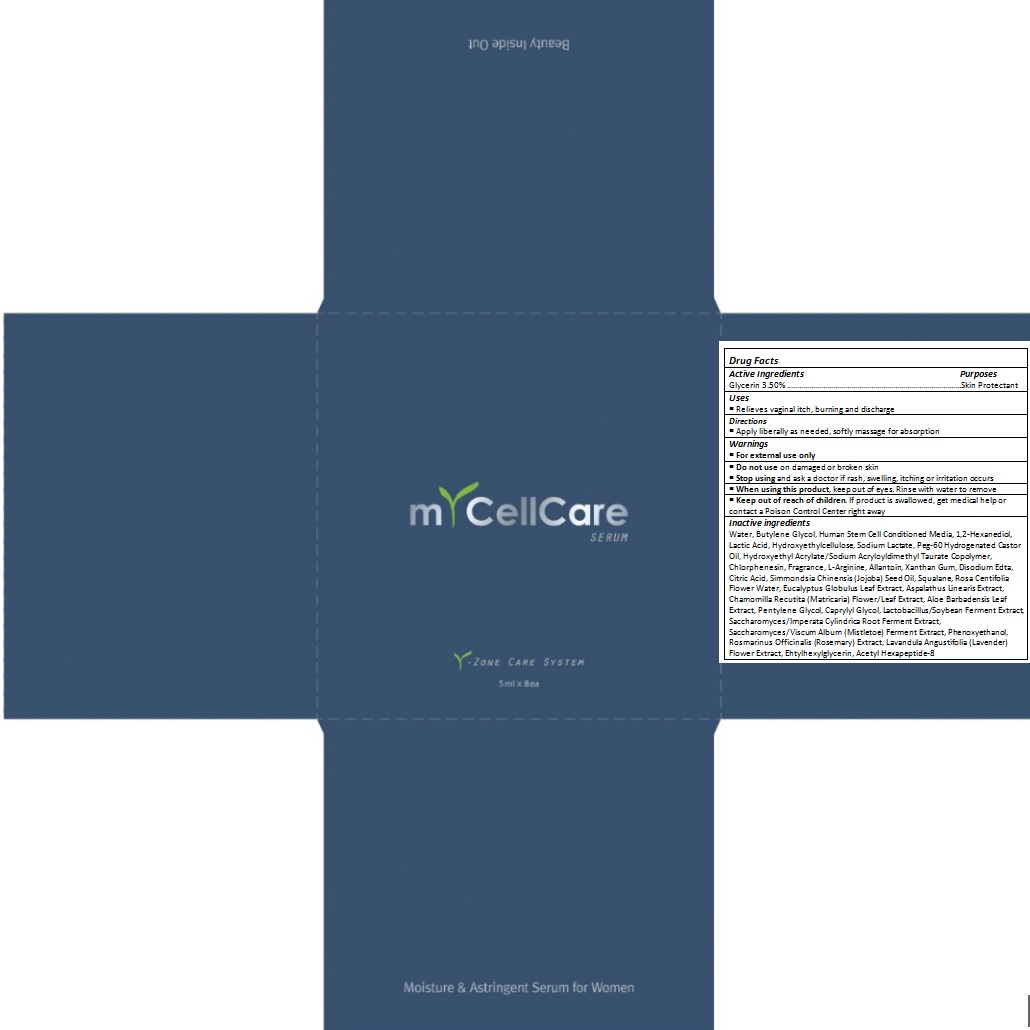 DRUG LABEL: myCellCare
NDC: 24765-105 | Form: CREAM
Manufacturer: Pharmacal-International. Co., Ltd.
Category: otc | Type: HUMAN OTC DRUG LABEL
Date: 20241025

ACTIVE INGREDIENTS: GLYCERIN 0.175 mg/5 mL
INACTIVE INGREDIENTS: WATER; BUTYLENE GLYCOL; 1,2-HEXANEDIOL; LACTIC ACID, UNSPECIFIED FORM; HYDROXYETHYL CELLULOSE (100 MPA.S AT 2%); SODIUM LACTATE; PEG-60 HYDROGENATED CASTOR OIL; HYDROXYETHYL ACRYLATE/SODIUM ACRYLOYLDIMETHYL TAURATE COPOLYMER (100000 MPA.S AT 1.5%); CHLORPHENESIN; ARGININE; ALLANTOIN; XANTHAN GUM; EDETATE DISODIUM; CITRIC ACID MONOHYDRATE; JOJOBA OIL; SQUALANE; ROSA CENTIFOLIA FLOWER OIL; EUCALYPTUS GLOBULUS LEAF; ASPALATHUS LINEARIS LEAF; MATRICARIA RECUTITA FLOWERING TOP; ALOE VERA LEAF; PENTYLENE GLYCOL; CAPRYLYL GLYCOL; VISCUM ALBUM FRUITING TOP; PHENOXYETHANOL; ROSEMARY; LAVANDULA ANGUSTIFOLIA FLOWER; ETHYLHEXYLGLYCERIN; ACETYL HEXAPEPTIDE-8

Drug Facts

ACTIVE INGREDIENT

Glycerin 3.50%

PURPOSE

Skin protectant

INDICATIONS AND USAGE

Relieves vaginal itch, burning and discharge

DOSAGE AND ADMINISTRATION

Apply liberally as needed, softly massage for absorption

WARNINGS

For external use only

Do not use on damaged or broken skin

When using this product, keep out of eyes. Rinse with water to remove.

Stop using and ask a doctor if rash, swelling, or irritation occurs.

KEEP OUT OF REACH OF CHILDREN

Keep out of reach of the children. If product is swallowed, get medical help or contact a poison control center right away.

INACTIVE INGREDIENT

Water, Butylene Glycol, Human Stem Cell Conditioned Media, 1,2-Hexanediol, Lactic Acid, Hydroxyethylcellulose, Sodium Lactate, Peg-60 Hydrogenated Castor Oil, Hydroxyethyl Acrylate/Sodium Acryloyldimethyl Taurate Copolymer, Chlorphenesin, Fragrance, L-Arginine, Allantoin, Xanthan Gum, Disodium Edta, Citric Acid, Simmondsia Chinensis (Jojoba) Seed Oil, Squalane, Rosa Centifolia Flower Water, Eucalyptus Globulus Leaf Extract, Aspalathus Linearis Extract, Chamomilla Recutita (Matricaria) Flower/Leaf Extract, Aloe Barbadensis Leaf Extract, Pentylene Glycol, Caprylyl Glycol, Lactobacillus/Soybean Ferment Extract, Saccharomyces/Imperata Cylindrica Root Ferment Extract, Saccharomyces/Viscum Album (Mistletoe) Ferment Extract, Phenoxyethanol, Rosmarinus Officinalis (Rosemary) Extract, Lavandula Angustifolia (Lavender) Flower Extract, Ehtylhexylglycerin, Acetyl Hexapeptide-8